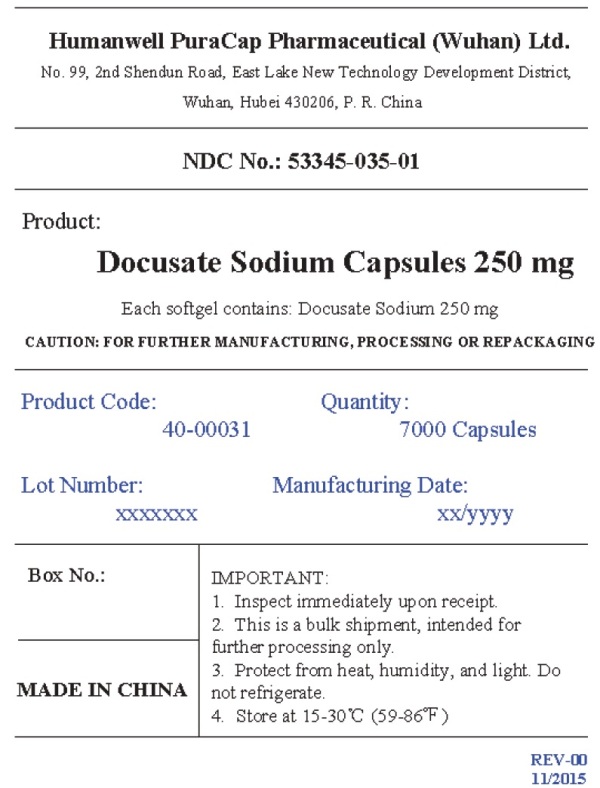 DRUG LABEL: Docusate Sodium
NDC: 53345-035 | Form: CAPSULE, LIQUID FILLED
Manufacturer: Humanwell PuraCap Pharmaceuticals (Wuhan) Co., Ltd
Category: otc | Type: HUMAN OTC DRUG LABEL
Date: 20241121

ACTIVE INGREDIENTS: DOCUSATE SODIUM 250 mg/1 1
INACTIVE INGREDIENTS: ANHYDROUS CITRIC ACID; FD&C RED NO. 40; FD&C YELLOW NO. 6; GELATIN; GLYCERIN; POLYETHYLENE GLYCOL, UNSPECIFIED; PROPYLENE GLYCOL; WATER; SORBITOL

Drug Facts

Active ingredient (in each softgel)

Docusate sodium 250 mg

Purpose

Stool softener laxative

Uses

- for the prevention of dry, hard stools
- for relief of occasional constipation
- this product generally produces a bowel movement within 12 to 72 hours

Warnings

Do not use

if you are presently taking mineral oil, unless directed by a doctor.

Ask a doctor before use if you have

- stomach pain
- nausea
- vomiting
- noticed a sudden change in bowel habits that last over 2 weeks

Stop use and ask a doctor if

- you have rectal bleeding or fail to have a bowel movement after use of a laxative. These could be signs of a serious condition.
- you need to use a laxative for more than 1 week

If pregnant or breast-feeding,

ask a health professional before use.

Keep out of reach of children.

In case of overdose, get medical help or contact a Poison Control Center right away.

Directions

- adults and children 12 years of age and over: take 1 softgel daily or as directed by a doctor
- children under 12 years of age: ask a doctor

Other information

- each softgel contains: sodium 15 mg
- store at 20º-25ºC(68º-77ºF); excursions permitted between 15º-30ºC (59º-86ºF)

Inactive Ingredients

citric acid anhydrous, FD&C red #40, FD&C yellow #6, gelatin, glycerin, polyethylene glycol, propylene glycol, purified water, sorbitol special, and white edible ink

Manufactured by:
Humanwell PuraCap Pharmaceutical (Wuhan) Co., Ltd.
Wuhan, Hubei 430206,
China

Principal Display Panel - Shipping Label

Docusate Sodium Capsules

250 mg

NDC 53345-035-01

7000 Capsules

IMPORTANT:
1.Inspect immediately upon receipt.
2.This is a bulk shipment, intended for further processing only.
3.Protect from heat, humidity, and light. Do not refrigerate.
4.Store at 15-30°C (59-86°F)

CAUTION : "FOR FURTHER MANUFACTURING, PROCESSING OR REPACKING"